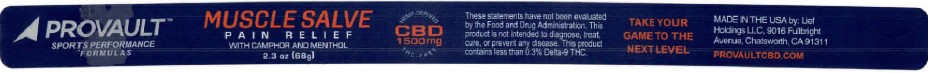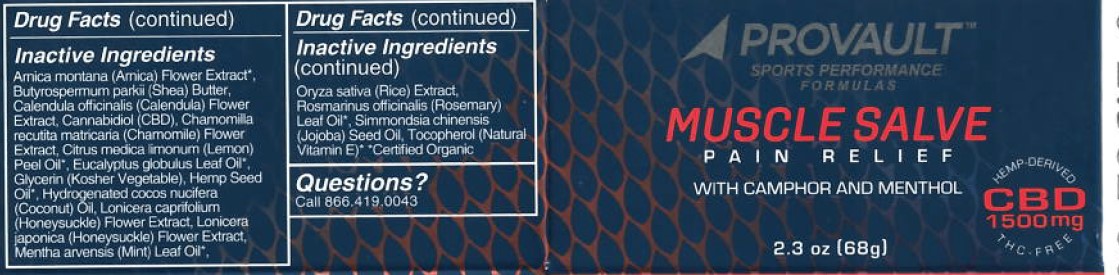 DRUG LABEL: Provault Muscle Salve
NDC: 61577-6300 | Form: GEL
Manufacturer: Sombra Cosmetics Inc
Category: otc | Type: HUMAN OTC DRUG LABEL
Date: 20221019

ACTIVE INGREDIENTS: MENTHOL .07 g/1 g; CAMPHOR (SYNTHETIC) .02 g/1 g
INACTIVE INGREDIENTS: SHEA BUTTER; HYDROGENATED COCONUT OIL; CARNAUBA WAX; CANNABIDIOL; TOCOPHEROL; JOJOBA OIL; ARNICA MONTANA FLOWER WATER; HEMP; LEMON OIL; EUCALYPTUS OIL; SPEARMINT OIL; ROSEMARY OIL; LONICERA JAPONICA FLOWER

Provault Muscle Salve

Active Ingredients

Menthol USP 7%, Camphor USP 2%

Purpose

External Analgesic

Keep out of reach of children

Uses

Temporary relief of monor aches and pains of muscles and joints associated with strains, bruises and sprains.

Warnings

For external use only.

Directions

Apply to affected area not more than 3 to 4 times daily. After each application, wash hands with soap and water (unless applying to hands). Children under the age of 18, consult a doctor before use.

Inactive Ingredients

Arnica Montana (Arnica) Flower Extract, Butyrospermum Parkii (Shea) Butter, Calendula officinalis (Calendula) Flower Extract, Cannabidiol (CBD), Chamomilla Recutita Matricaria (Chamomile) Flower Extract, Citrus Medica Limonum (Lemon) Peel Oil, Eucalyptus Globulus Leaf Oil, Glycerin, (Kosher Vegetable), Hemp Seed Oil, Hydrogenated Cocos Nucilera (Coconut) Oil, Lonicera Japonica (Honeysuckle) Flower Extract, Mentha Avensis (Mint) Leaf Oil.

Questions or Comments

Call 866 419 0043